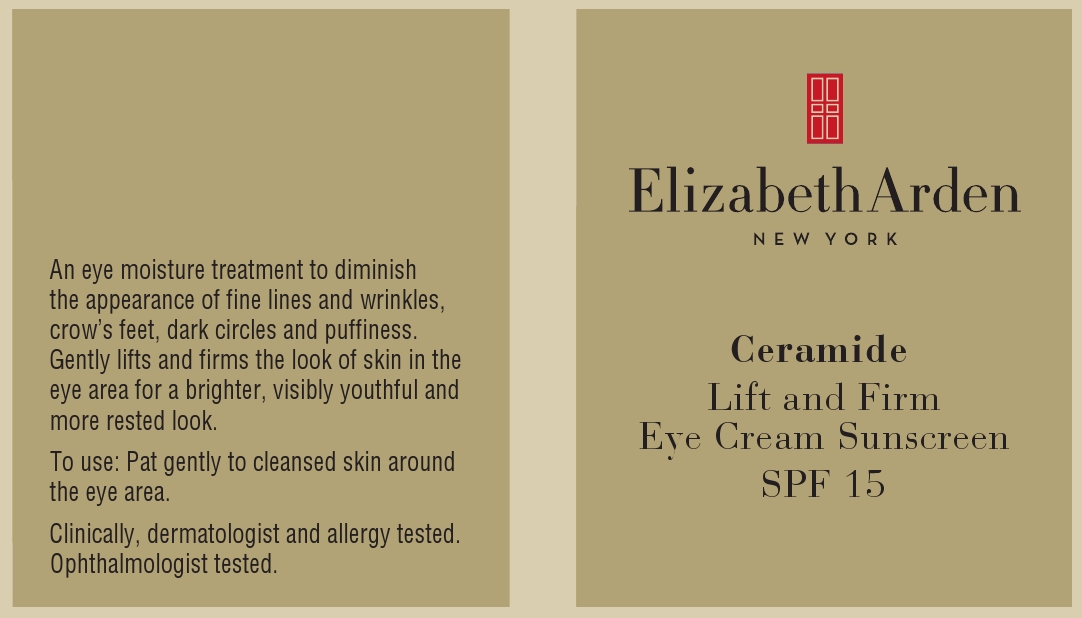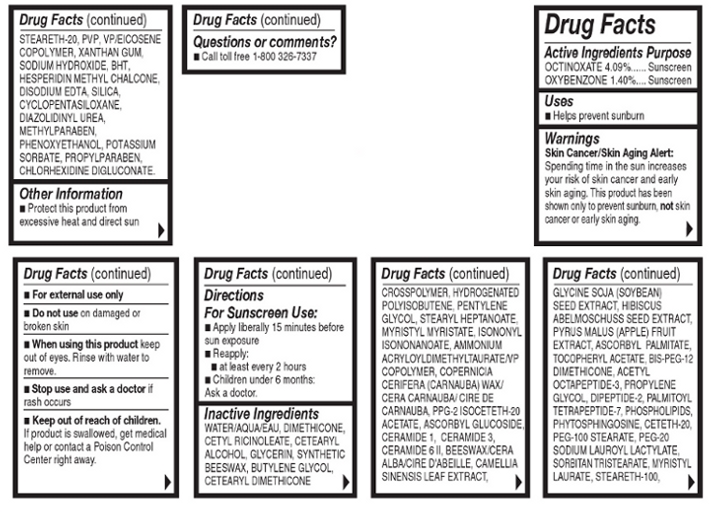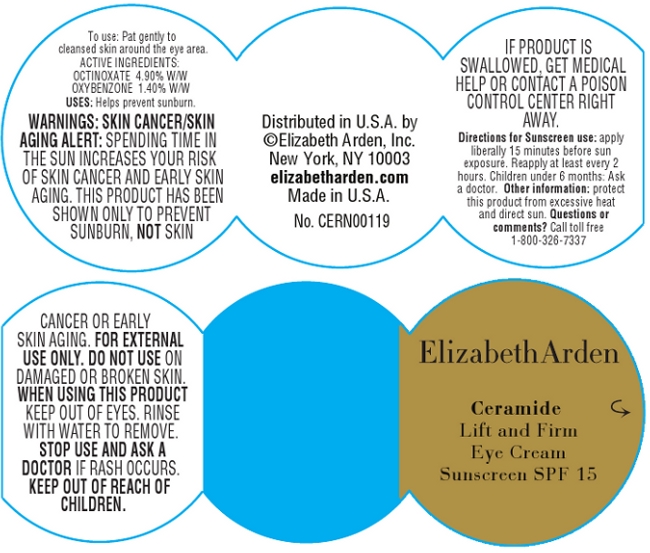 DRUG LABEL: Ceramide Lift And Firm Eye Sunscreen SPF 15
NDC: 67938-0993 | Form: CREAM
Manufacturer: Elizabeth Arden, Inc
Category: otc | Type: HUMAN OTC DRUG LABEL
Date: 20130416

ACTIVE INGREDIENTS: OCTINOXATE 0.58896 g/14.4 g; OXYBENZONE 0.2016 g/14.4 g
INACTIVE INGREDIENTS: WATER; DIMETHICONE; CETYL RICINOLEATE; CETOSTEARYL ALCOHOL; GLYCERIN; BUTYLENE GLYCOL; PENTYLENE GLYCOL; STEARYL HEPTANOATE; MYRISTYL MYRISTATE; ISONONYL ISONONANOATE; AMMONIUM ACRYLOYLDIMETHYLTAURATE/VP COPOLYMER; CARNAUBA WAX; PPG-2 ISOCETETH-20 ACETATE; CETETH-20; PHENOXYETHANOL; CYCLOMETHICONE 5; MYRISTYL LAURATE; PEG-100 STEARATE; ASCORBYL GLUCOSIDE; YELLOW WAX; SORBITAN TRISTEARATE; STEARETH-100; ABELMOSCHUS MOSCHATUS SEED; PROPYLENE GLYCOL; BUTYLATED HYDROXYTOLUENE; DIAZOLIDINYL UREA; EDETATE DISODIUM; HESPERIDIN METHYLCHALCONE; SODIUM HYDROXIDE; STEARETH-20; APPLE; GREEN TEA LEAF; METHYLPARABEN; SODIUM LAUROYL LACTYLATE; XANTHAN GUM; SILICON DIOXIDE; PROPYLPARABEN; SOYBEAN; CERAMIDE 3; CHLORHEXIDINE GLUCONATE; OMEGA-3 FATTY ACIDS; CERAMIDE 6 II; VALYLTRYPTOPHAN; PHYTOSPHINGOSINE; POTASSIUM SORBATE; .ALPHA.-TOCOPHEROL ACETATE; ASCORBYL PALMITATE; PALMITOYL TETRAPEPTIDE-7; CERAMIDE 1

BC0993

DESCRIPTION

An eye moisture treatment to diminish the appearance of fine lines and wrinkles, crow's feet, dark circles, and puffiness. Gently lifts and firms the look of skin in the eye area for a brighter, visibly youthful, and more rested look.

INDICATIONS AND USAGE

To Use: Pat gently to cleansed skin around the eye area.

For Sunscreen Use: Apply liberally 15 minutes before sun exposure. Reapply at least every 2 hours.

WARNINGS

Skin Cancer/Skin Aging Alert: Spending time in the sun increases your risk of skin cancer and early skin aging. This product has been shown only to prevent sunburn, not skin cancer or early skin aging.

For external use only.

Do not use on damaged or broken skin.

When using this product, keep out of eyes. Rinse with water to remove.

Stop use and ask a doctor if rash occurs.

OTC - ACTIVE INGREDIENT

Active Ingredients: Octinoxate 4.09%, Oxybenzone 1.40%.

INACTIVE INGREDIENT

Othe Ingredients: Water/Aqua/Eau, Dimethicone, Cetyl Ricinoleate, Octinoxate, Cetearyl Alcohol, Glycerin, Synthetic Beeswax, Butylene Glycol, Stearyl Heptanoate, Myristal Myristate, Isononyl Isononanoate, Oxybenzone, Ammonium Acryloyldimethyltaurate/VP Copolymer, Copernicia Cerifera (Carnauba) Wax/Cera Carnauba/Cire de Carnauba, PPG-2 Isoceteth-20 Acetate, Ceteth-20, Penoxyethanol, Cyclopentasiloxane, Myristyl Laurate, PEG-100 Stearate, Ascorbyl Glucoside, Beeswax/Cera Alba/Cire d'Abeille, BIS-PEG-12 Dimethicone, PEG-20, Sorbitan Tristearate, Steareth-100, Hibiscus Abelmoschuss Seed Extract, Propylene Glycol, VP/Eicosense Copolymer, BHT, Diazolidnyl Urea, Disodium EDTA, Hesperidin Methyl Chalcone, Sodium Hydroxide, Steareth-20, Pyrus Malus (Apple) Fruit Extract, Camellia Sinensis Leaf Extract, Methylparaben, Sodium Lauroyl Lactylate, Xanthan Gum, Silica, Propylparaben, Glycine Soja (Soybean) Seed Extract, PVP, Ceramide 3, Chlorhexdine Digluconate, Phospholipids, Ceramide 6 II, Dipeptide-2, Phytosphingosine, Potassium Sorbate, Tocopheryl Acetate, Ascorbyl Palmitate, Palmitoyl Tetrapeptide-7, Acetyl Octapeptide-3, Ceramide 1.

DOSAGE & ADMINISTRATION

Pat around eyes.

OTC - KEEP OUT OF REACH OF CHILDREN

Keep out of reach of children. If product is swallowed, get medical help or contact a Poison Control center immediately.

OTC - PURPOSE

Provides SPF 15 sun protection.

OTC - WHEN USING

Keep out of eyes.